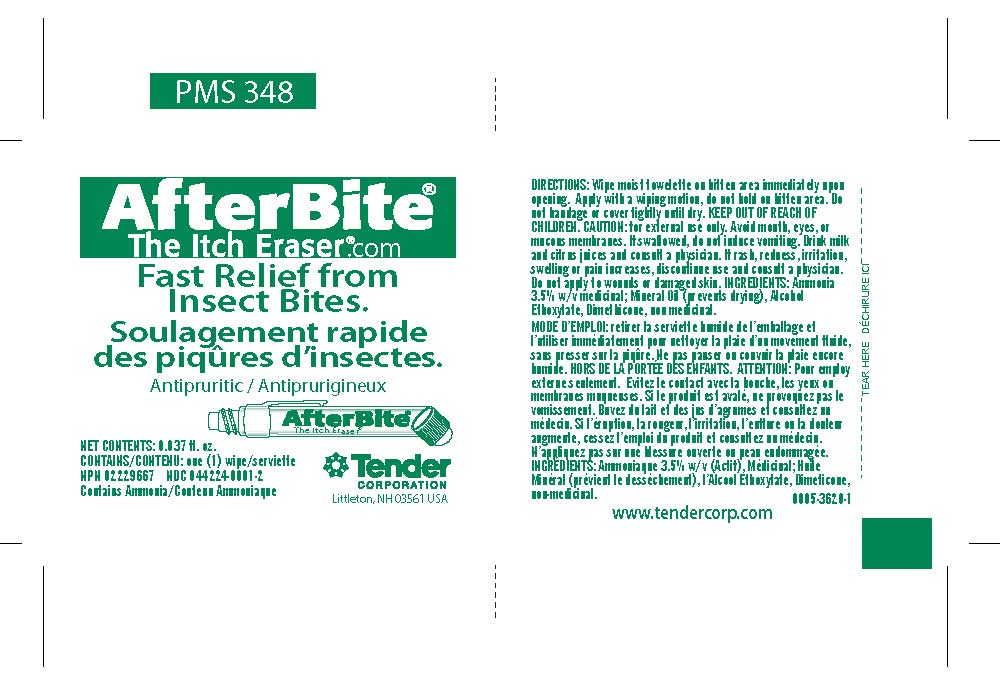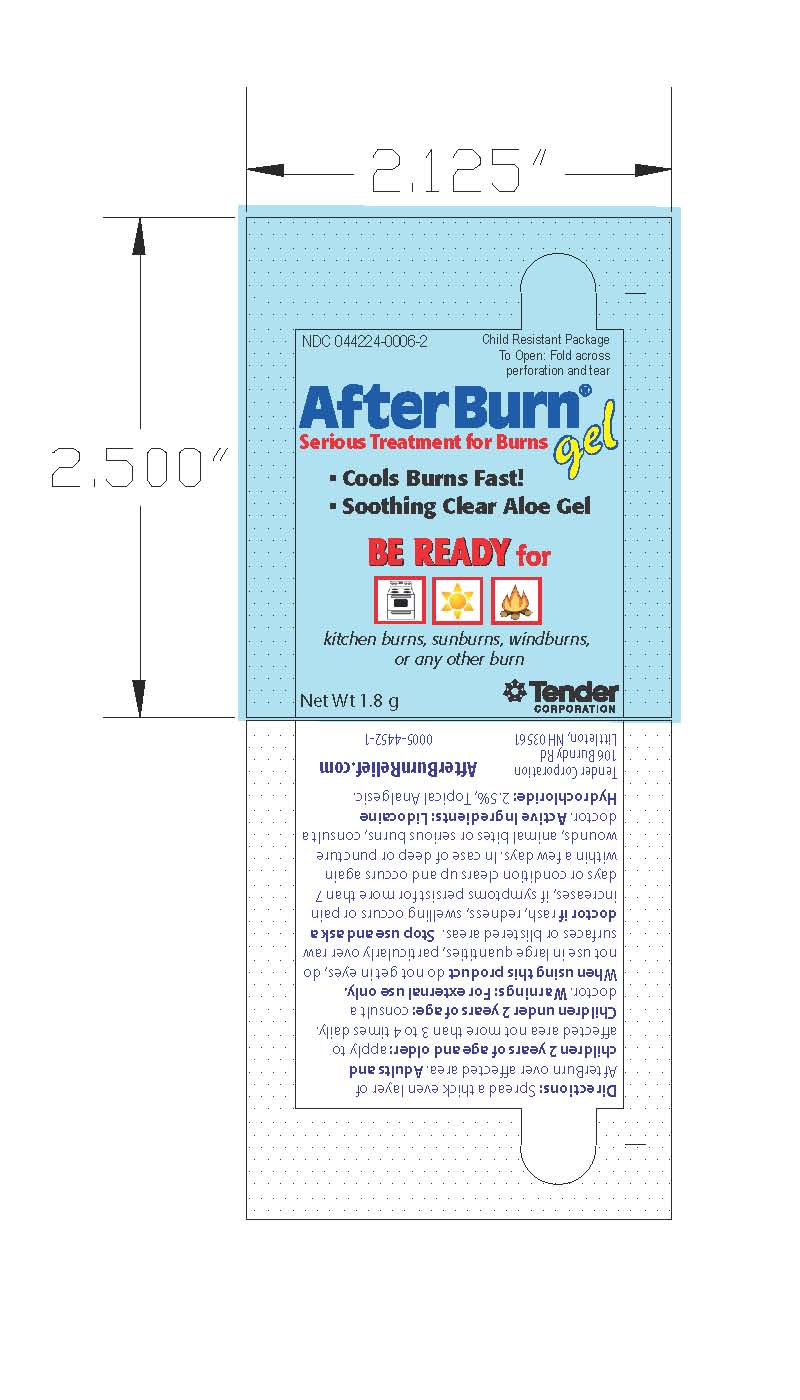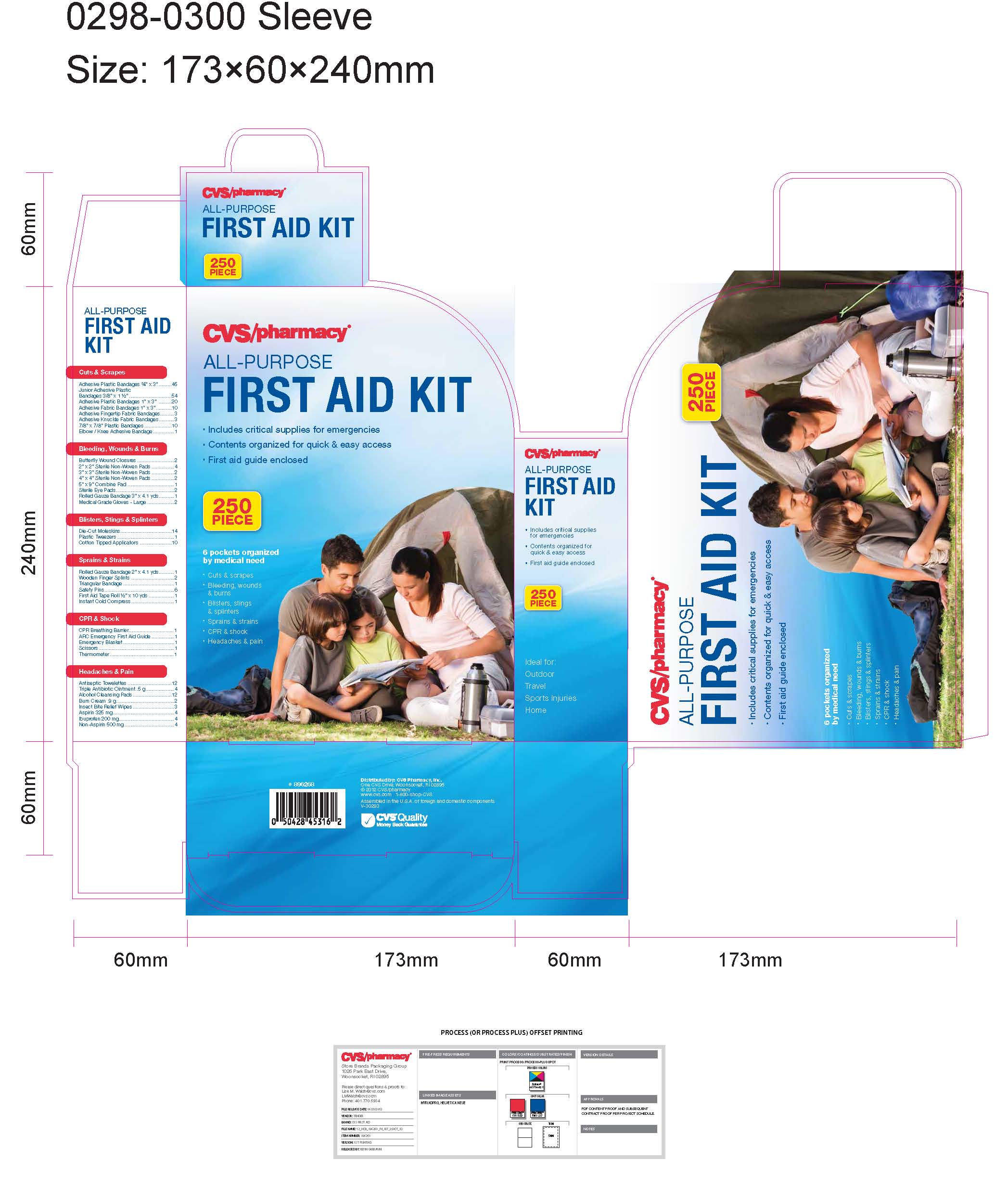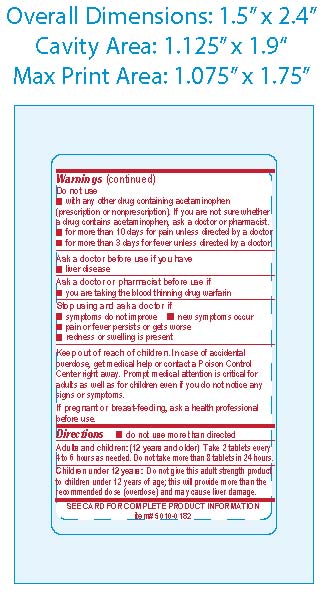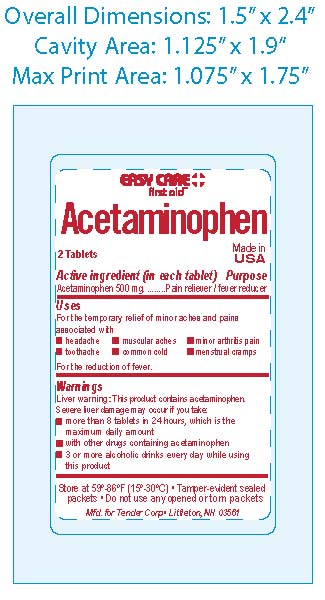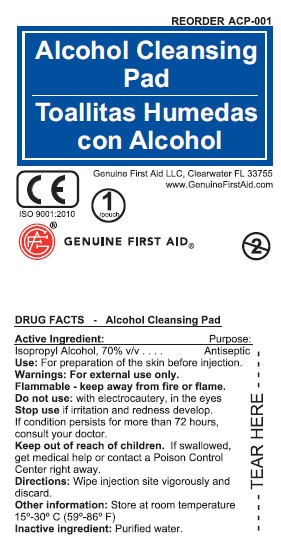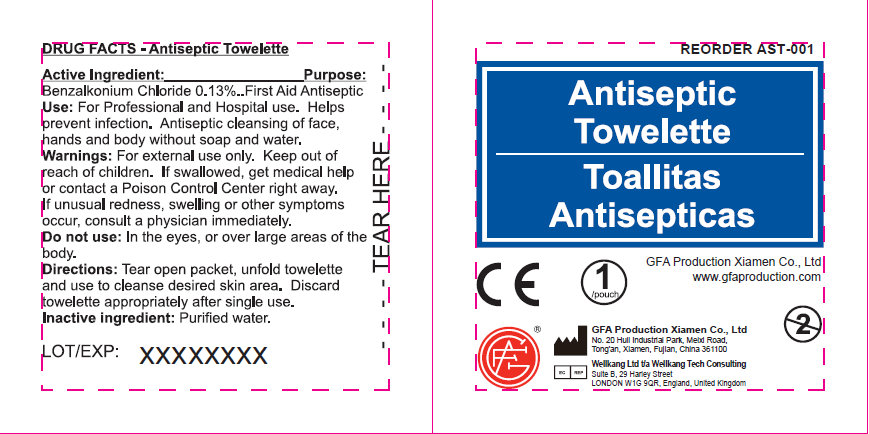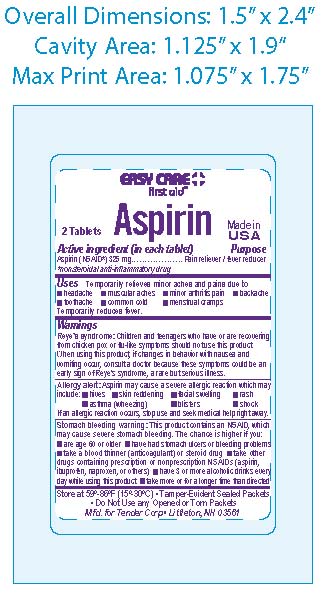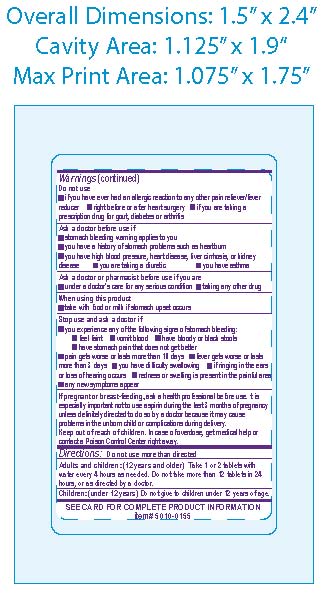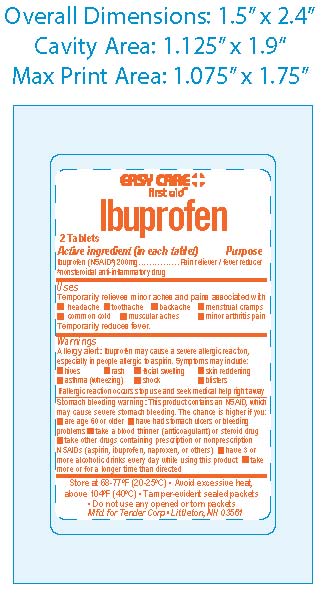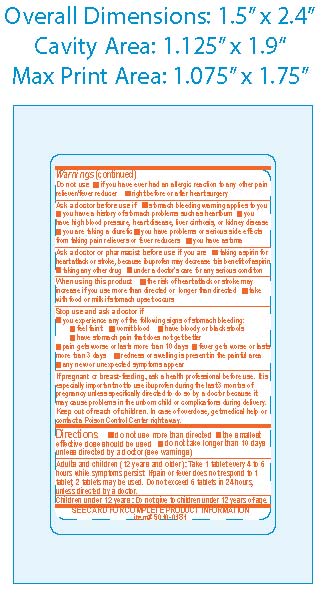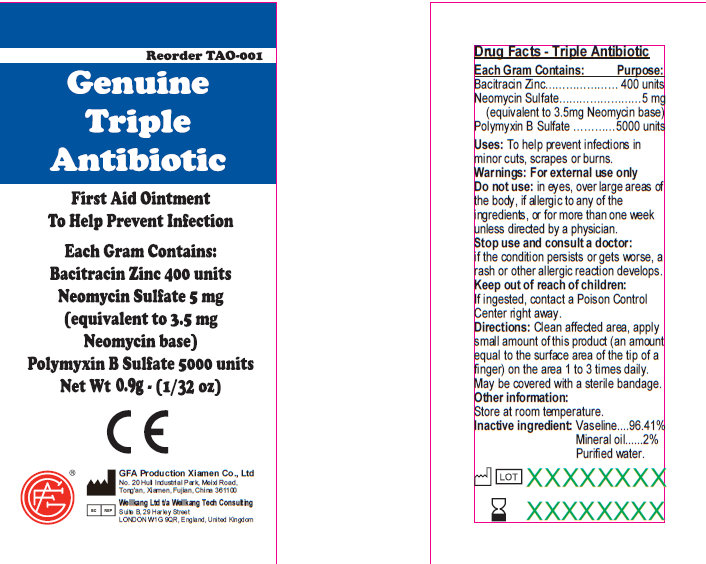 DRUG LABEL: CVS All Purpose First Aid Kit
NDC: 69842-300 | Form: KIT | Route: TOPICAL
Manufacturer: CVS
Category: otc | Type: HUMAN OTC DRUG LABEL
Date: 20170221

ACTIVE INGREDIENTS: AMMONIA 30 mg/1 mL; LIDOCAINE HYDROCHLORIDE 25 mg/1 mL; ACETAMINOPHEN 500 mg/1 1; IBUPROFEN 200 mg/1 1; BENZALKONIUM CHLORIDE 1.3 mg/1 mL; BACITRACIN ZINC 400 [iU]/1 g; NEOMYCIN SULFATE 5 mg/1 g; POLYMYXIN B SULFATE 5000 [iU]/1 g; ASPIRIN 325 mg/1 1; ISOPROPYL ALCOHOL 700 mg/1 mL
INACTIVE INGREDIENTS: LIGHT MINERAL OIL; C12-13 ALCOHOLS; WATER; DIMETHICONE 1000; CARBOMER HOMOPOLYMER TYPE C; POLYSORBATE 20; WATER; SODIUM HYDROXIDE; ALOE VERA LEAF; BENZALKONIUM CHLORIDE; GLYCERIN; MENTHOL; HYPROMELLOSES; POLYETHYLENE GLYCOLS; CELLULOSE, MICROCRYSTALLINE; MALTODEXTRIN; POVIDONE; SODIUM STARCH GLYCOLATE TYPE A POTATO; STARCH, CORN; STEARIC ACID; POVIDONE K30; POLYETHYLENE GLYCOLS; STEARIC ACID; STARCH, CORN; TITANIUM DIOXIDE; SILICON DIOXIDE; FERRIC OXIDE RED; SODIUM STARCH GLYCOLATE TYPE A POTATO; POLYVINYL ALCOHOL, UNSPECIFIED; TALC; WATER; PETROLATUM; WATER; MINERAL OIL; MINERAL OIL; CELLULOSE, MICROCRYSTALLINE; CROSCARMELLOSE SODIUM; HYPROMELLOSES; TITANIUM DIOXIDE; STARCH, CORN; WATER

CVS All Purpose First Aid Kit

Active Ingredients - Genuine Triple Antibiotic

Active Ingredient: .........Bacitracin Zinc 400 units

Neomycin Sulfate 5mg (equivalent to 3.5 mg Neomycin base)

Polymyxin B Sulfate 5000 units

Purpose - Genuine Triple Antibiotic

Triple Antibiotic

Uses - Genuine Triple Antibiotic

To help prevent infection in:
minor cuts; scrapes; burns

Warnings - Genuine Triple Antibiotic

For external use only

DO NOT USE - Genuine Triple Antibiotic

Do not use: in eyes; over large areas of the body;

If allergic to any of the ingredients; for more than one week unless directed by a physician.

Stop Use - Genuine Triple Antibiotic

Stop use and consult a doctor:

if the condition persists or gets worse; a rash or other allergic reaction develops

Keep Out of Reach of Children - Genuine Triple Antibiotic

Keep out of reach of children.

If ingested, contact a Poison

Control Center right away.

Directions - Genuine Triple Antibiotic

Directions: clean affected area; apply small amount of this product (an amount equal to the surface area of the tip of a finger) on the area 1 to 3 times daily; may be covered with a sterile bandage

Storage and Handling - Genuine Triple Antibiotic

Other information:

Store at room temperature.

Inactive Ingredients - Genuine Triple Antibiotic

Vaseline
Mineral Oil
Purified Water

Active Ingredients - Antiseptic

Active Ingredient:

Benzalkonium Chloride 0.13

Purpose - Antiseptic

Antiseptic

Use - Antiseptic

For Professional and Hospital use. Helps prevent infection. Antiseptic cleansing of face, hands and body without soap and water.

Warnings - Antiseptic

Warning: For external use only.

Keep out of reach of children - Antiseptic

Keep out of reach of children: If swallowed, get medical help or contact a Poison Control Center right away.

Stop Use - Antiseptic

Stop use if unusual redness, swelling or other symptoms occur. Consult a physician immediately.

Do Not Use - Antiseptic

Do not use in the eyes or over large areas of the body.

Directions - Antiseptic

Tear open packet, unfold towelette and use to cleanse desired skin area. Discard towelette appropriately after single use.

Inactive Ingredients - Antiseptic

Inactive Ingredient: Purified water

Active Ingredient - Ibuprofen

Ibuprofen USP (NSAID*) 200mg
*nonsteroidal anti-inflammatory drug

Purpose - Ibuprofen

Pain reliever/fever reducer

Uses - Ibuprofen

temporarily relieves minor aches and pains due to:
the common cold
headache
toothache
muscular aches
backache
minor pain of arthritis
menstrual cramps temporarily reduces fever

Warnings - Ibuprofen

Allergy alert : Ibuprofen may cause a severe allergic reaction, especially in people allergic to aspirin. Symptoms may include: shock, facial swelling, asthma (wheezing) rash, skin reddening, blisters, hives If an allergic reaction occurs, stop use and seek medical help right away.
Stomach bleeding warning: This product contains a nonsteroidal anti-inflammatory drug (NSAID), which may cause severe stomach bleeding. The chance is higher if you: are age 60 or older, have had stomach ulcers or bleeding problems, take a blood thinner (anticoagulant) or steroid drug, take other drugs containing NSAIDs (aspirin, ibuprofen, naproxen, or others), have 3 or more alcoholic drinks every day while using this product, take more or for a longer time than directed

Do Not Use - Ibuprofen

Do not use if you have ever had an allergic reaction to any other pain reliever/fever reducer, right before or after heart surgery.

Ask a Doctor - Ibuprofen

Ask a doctor before use if stomach bleeding warning applies to you; you have a history of stomach problems such as heartburn; you have a high blood pressure, heart disease, liver cirrhosis, or kidney disease; you are taking a diuretic

Ask a doctore before use if you are taking any other drug containing NSAID (prescription or nonprescription); taking aspirin for heart attack or stroke, because Ibuprofen may decrease this benefit of aspirin; taking any other drug

When Using - Ibuprofen

when using this product take with food or milk if stomach upset occurs

Stop Use - Ibuprofen

Stop use and ask a doctor if you experience any of the following signs of stomach bleeding; feel faint; vomit blood; have bloody or black stools; have stomach pain that does get better; pain gets worse or lasts more than 10 days; fever gets worse or lasts more than 3 days; redness or swelling is present in the painful area; any new symptoms appear

Pregnancy or Breast Feeding - Ibuprofen

If pregnant or breast-feeding, ask a health professional before use. It is especially important not to use ibuprofen during the last 3 months of pregnancy unless definitely directed to do so by a doctor because it may cause problems in the unborn child or complications during delivery.

Keep out of reach of Children - Ibuprofen

Keep out of reach of children. In case of overdose, get medical help or contact a Poison Control Center right away.

Directions - Ibuprofen

do not use more than directed; the smallest effective dose should be used; do not take longer than 10 days, unless directed by a doctor.
Adults and Children (12 years and older): Take 1 tablet every 4 to 6 hours while symptoms persist. If pain or fever does not respond to 1 tablet, 2 tablets may be used. Do not exceed 6 tablets in 24 hours, unless directed by a doctor.
Children under 12 years: Do not give to children under 12 years of age.

Other Information

Store at controlled room temperature; avoid excessive heat 40 degree Celsius (104 degree Fahrenheit); tamper evident sealed packets; do not use any opened or torn packets

Active Ingredients - Non-Aspirin

Acetaminophen 500 mg

Purpose - Non Aspirin

Analgesic/antipyretic

Uses - Non Aspirin

temporary relief of minor aches and pains associated with:

common cold; headache; toothache; muscular aches; backache; arthritis; menstrual cramps; and reduction of fever

Warnings - Non Aspirin

Liver warning: This product contains acetaminophen.

Severe liver damage may occur if: adult takes more than 12 tablets in 24 hours, which is the maximum daily amount; child takes more than 5 doses in 24 hours; taken with other drugs containing acetaminophen; adult has 3 or more alcoholic drinks every day while using this product

Do Not Use - Non Aspirin

with any other drug containing acetaminophen (prescription or nonprescription). If you are not sure whether a drug contains acetaminophen, ask a doctor or pharmacist; for more than 10 days for pain unless directed by a doctor; for more than 3 days for fever unless directed by a doctor

Ask a Doctor - Non Aspirin

Ask a doctor before use if the user has liver disease

Ask a doctor or pharmacist before use if the user is taking the blood thinning drug warfarin

Stop Use - Non Aspirin

Stop use and ask a doctor if: symptoms do not improve; pain gets worse or lasts for more than 10 days; fever gets worse or lasts for more than 3 days; new symptoms occur; redness or swelling is present; a rare sensitivity reaction occurs

Pregnancy - Non Aspirin

If pregnant or breast-feeding, ask a health professional before use.

Keep Out of Reach of Children - Non Aspirin

Keep out of reach of children. In case of accidental overdose, contact a doctor or Poison Control Center immediately. Prompt
medical attention is critical for adults as well as for children even if
you do not notice any signs or symptoms. Do not exceed recommended dosage

Directions - Non Aspirin

Directions

Adults and Children Take 2 tablets every 4 to 6 hours as

12 years of age needed. Do not take more than 12 tablets

or older in 24 hours.

Children 6-11 years Take 1 tablet every 4 to 6 hours as

of age needed. Do not take more than 5

tablets in 24 hours.

Children under 6 Do not use this regular strength product.

years of age This will provide more than the

recommended dose (overdose) and could

cause serious health problems.

Storage and Handling - Non Aspirin

Store at 59-86 degree F (15-30 degree C)

tamper evident sealed packets; do not use any open or torn packets

Active Ingredients - Burn Cream

ACTIVE INGREDIENTS:
Lidocaine HCL 2.5%

Purpose - Burn Cream

Purpose: First aid antiseptic, external analgesic

Uses - Burn Cream

First aid to help prevent infection and for the temporary relief of pain and itching associated with:

Minor Cuts

Scrapes

Burns

Warnings - Burn Cream

For external use only

Do Not Use - Burn Cream

Do not use: In eyes, in large quantities, over raw blistered areas, or on deep puncture wounds, animal bites or serious burns, for more than one week
Do not use:
in the eyes or apply over large areas of the body.
longer than 1 week unless directed by a doctor.
in large quantities, particularly over raw surfaces or blistered areas.
Ask a doctor before use if you have deep puncture wounds, animal bites or serious burns.
When using this product, avoid contact with the eyes.

Stop Use - Burn Cream

Stop use and ask a doctor if
condition worsens
symptoms persist for more than 7 days
condition clears up and occurs again within a few days

Keep Out of Reach of Children

If ingested, contact a Poison Control Center right away.

Directions - Burn Cream

Adults and children 2 years of age and older

clean affected area.

apply a small amount of this product on the area 1 to 3 times daily.

may be covered with a sterile bandage

children under 2 years of age: consult a doctor

Storage and Handling - Burn Cream

Other Information:
Store at room temperature (do not freeze).

Taper evident sealed packets.

Do not use packet if opened or torn.

Active Ingredients - After Bite

Active Ingredient:

Ammonia 3.5%

Purpose - After Bite

Counterirritant

Uses - After Bite

Temporarily protects and helps relieve minor skin irriatation and itching due to

- insect bites and stings
- poison ivy, oak or sumac

Warnings - After Bite

Warning: For external use only.

Keep Out of Reach of Children - After Bite

Keep out of reach of children: If swallowed, get medical help or contact a Poison Control Center right away.

Stop Use - After Bite

Stop use and ask a doctor if

- condition worsens
- symptoms last more than 7 days or clear up and occur again within a few days

When Using - After Bite

Do not get into eyes

DIrections - After Bite

Adults and children under 2 years and older dab directly on bite or sting, rub gently and re-apply as needed

Children under 2 years ask a doctor

Active Ingredient - Aspirin

Aspirin (NSAID*) 325mg

*nonsteroidal anti-inflammatory drug

Purpose

Pain Releiver / Fever Reducer

Uses - Aspirin

Temporarily relieves minor aches and pains associated with: headache; muscular aches; minor arthritis pain; backache; common cold; toothache; mentrual cramps; temporarily reduces fever

Warnings

Reye's syndrome: Children and teenagers who have or are recovering from chicken pox of flu-like symptoms should not use this product. When using this product, if changes in behavior with nausea and vomiting occur, consult a doctor because these symptoms could be an early sign of Reye's syndrome, a rare but serious illness.

Allergy Alert: Aspirin may cause a severe allergic reaction which may include: hives, skin reddening, facial swelling, rash, asthma (wheezing), blisters, shock. If an allergic reaction occurs, stop use and seek medical help right away.

Stomach bleeding warning: This contains an NSAID, which may cause severe stomach bleeding. The change is higher if you: are age 60 or older; have had stomach ulcers or bleeding problems; take a blood thinner (anticoagulant) or steroid drug; take other drugs containing prescription or nonprescription NSAIDs (aspirin, ibuprofen, naproxen, or others), have 3 or more alcoholic drinks everyday while using this product, take more for a longer time than directed

Do Not Use - Aspirin

Do not use if you have ever had an allergic reaction to any other pain reliever/fever reducer; right before or after heart surgery; if you are taking a prescription drug for gout, diabetes or arthritis.

Ask a doctor before use if: stomach bleeding warning applies to you; you have a history of stomach problems such as heartburn; you have high blood pressure, heart disease, liver cirrhosis or kidney disease; you are taking a diuretic.

Ask a doctor or pharmacist before use if you are: under a doctor's care for any serious condition; taking any other drug.

When using this product: Take with food or milk if stomach upset occurs.

Stop Use and ask a Doctor - Aspirin

Stop Use and ask a Doctor if:

You experience any of the following signs of stomach bleeding, you feel faint, vomit blood, have bloody or black stools, have stomach pain that does not get better, pain gets worse or lasts more than 10 days, fever gets worse or lasts more than 3 days, you have difficulty swallowing, if ringing in the ears or loss of hearing occurs, redness or swelling is present in painful areas, or any new symptoms appear.

If pregnant or breast-feeding, ask a health professional before use. It is especially important not to use aspirin during the last 3 months of pregnancy unless directed to do so by a doctor because it may cause problems in the unborn child or complications during delivery.

Keep out of reach of Children. In case of overdose, get medical help or contact a poison control center right away.

Directions - Aspirin

Do not use more than directed - the smallest effective dose should be used.

Drink a full glass of water with each dose.

Do not take longer than 10 days, unless directed by a doctor.

Adults and Children (12 years and older): take 1 or 2 tablets with water every 4 hours as needed. Do not take more then 12 tablets in 24 hours, or as directed by a doctor.

Children under 12 years: Do not give to children under 12 years of age.

Avoid excessive heat and humidity, do not use any open or torn packets.

Principal Display Panel - Triple Antibiotic

Genuine Triple Antibiotic

First Aid Ointment

To Help Prevent Infection

Each Gram Contains:

Bacitracin Zinc 400 units

Neomycin Sulfate 5 mg

(equivalent to 3.5 mg

Neomycin base)

Polymyxin B Sulfate 5000 units

Net Wt. 0.5g ; (1/64 oz)

Manufactured in CHINA for

GENUINE FIRST AID.

Package Label - Antiseptic

Antiseptic Towelette

Genuine First Aid LLC, Clearwater FL 33755

www.GenuineFirstAid.com

1/pouch

GENUINE FIRST AID

Package Label - Burn Cream

Genuine First Aid Burn Cream
Antiseptic Pain Relief With Aloe
Net Wt 0.9g (1/32 oz)
Manufactured in CHINA for
Genuine First Aid

GFA Production Xiamen Co., Ltd
No. 20 Huli Industrial Park, Meixi Road, Tong'an, Xiamen, Fujian, China 361100
Tel: 86-592-7269515 Fax: 86-592-7269528 Http: //www.gfaproduction.com

Package Label - After Bite

After Bite

The Itch Eraser

Fast Relief from Insect Bites.

Net Contents: 0.037fl. oz.

Contains: One (1) Wipe

Contains Ammonia

Tender Corporation

Littleton, NH 03561